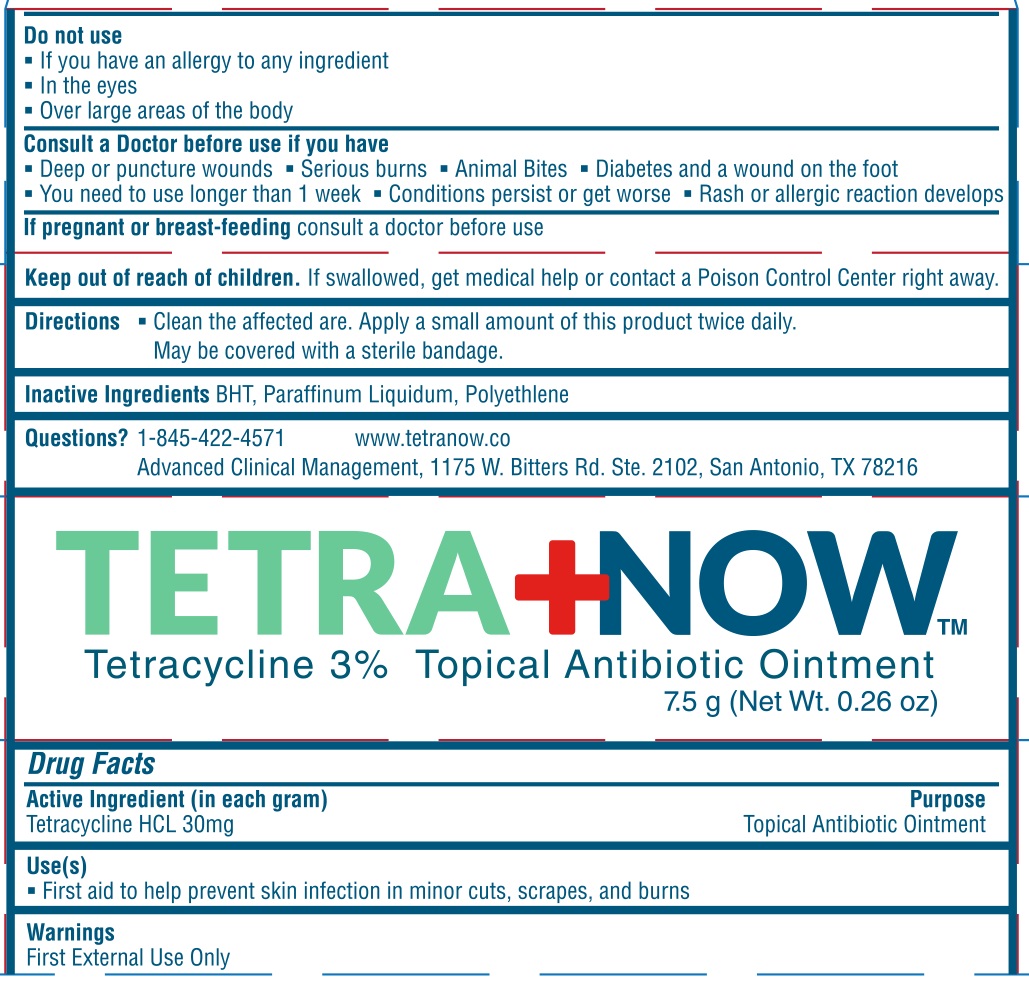 DRUG LABEL: TETRA NOW
NDC: 81871-101 | Form: OINTMENT
Manufacturer: ADVANCED CLINICAL MANAGEMENT LLC
Category: otc | Type: HUMAN OTC DRUG LABEL
Date: 20211202

ACTIVE INGREDIENTS: TETRACYCLINE HYDROCHLORIDE 3 g/100 g
INACTIVE INGREDIENTS: BUTYLATED HYDROXYTOLUENE; HIGH DENSITY POLYETHYLENE; MINERAL OIL

ADV CLINICAL MGMT - TETRA+NOW (81871-101)

ACTIVE INGREDIENT

TETRACYCLINE HCL 30 MG

PURPOSE

TOPICAL ANTIBIOTIC OINTMENT

USE(S)

- FIRST AID TO HELP PREVENT SKIN INFECTION IN MINOR CUTS, SCRAPES, AND BURNS

WARNINGS

FOR EXTERNAL USE ONLY.

DO NOT USE

- IF YOU HAVE AN ALLERGY TO ANY INGREDIENT
- IN THE EYES
- OVER LARGE AREAS OF THE BODY

CONSULT A DOCTOR BEFORE USE IF YOU HAVE

- DEEP OR PUNCTURE WOUNDS
- SERIOUS BURNS
- ANIMAL BITES
- DIABETES AND A WOUND ON THE FOOT
- YOU NEED TO USE LONGER THAN 1 WEEK
- CONDITIONS PERSIST OR GET WORSE
- RASH OR ALLERGIC REACTION DEVELOPS

IF PREGNANT OR BREAST-FEEDING CONSULT A DOCTOR BEFORE USE.

KEEP OUT OF REACH OF CHILDREN. IF SWALLOWED, GET MEDICAL HELP OR CONTACT A POISON CONTROL CENTER RIGHT AWAY.

DIRECTIONS

- CLEAN THE AFFECTED AREA. APPLY A SMALL AMOUNT OF THIS PRODUCT TWICE DAILY. MAY BE COVERED WITH A STERILE BANDAGE.

INACTIVE INGREDIENTS

BHT, PARAFINNUM LIQUIDUM, POLYETHYLENE

QUESTIONS?

1-845-422-4571

WWW.TETRANOW.CO

ADVANCED CLINICAL MANAGEMENT, 1175 W. BITTERS RD. STE. 2102, SAN ANTONIO, TX 78216